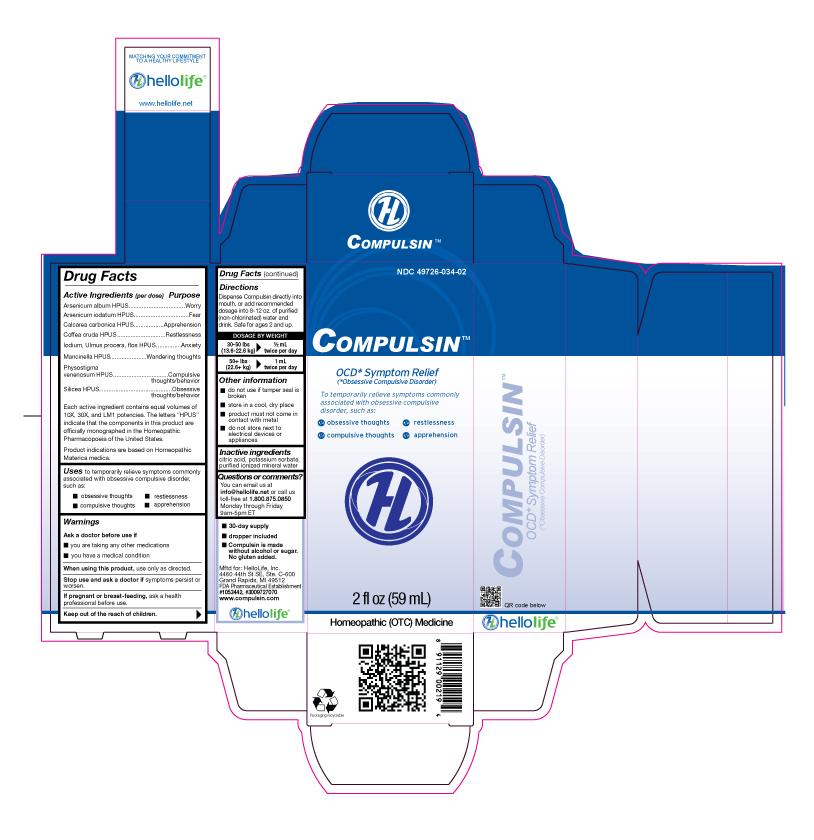 DRUG LABEL: Compulsin
NDC: 49726-034 | Form: LIQUID
Manufacturer: Hello Life, Inc.
Category: homeopathic | Type: HUMAN OTC DRUG LABEL
Date: 20181226

ACTIVE INGREDIENTS: ARSENIC TRIOXIDE 10 [hp_X]/59 mL; ARSENIC TRIIODIDE 10 [hp_X]/59 mL; OYSTER SHELL CALCIUM CARBONATE, CRUDE 10 [hp_X]/59 mL; ARABICA COFFEE BEAN 10 [hp_X]/59 mL; IODINE 10 [hp_X]/59 mL; ULMUS PROCERA FLOWERING TWIG 10 [hp_X]/59 mL; HIPPOMANE MANCINELLA FRUITING LEAFY TWIG 10 [hp_X]/59 mL; PHYSOSTIGMA VENENOSUM SEED 10 [hp_X]/59 mL; SILICON DIOXIDE 10 [hp_X]/59 mL
INACTIVE INGREDIENTS: CITRIC ACID MONOHYDRATE; POTASSIUM SORBATE; WATER

Drug Facts

Active Ingredients (per dose)

Arsenicum album HPUS

Arsenicum iodatum HPUS

Calcarea carbonica HPUS

Coffea cruda HPUS

Iodium, Ulmus procera, flos HPUS

Mancinella HPUS

Physostigma venenosum HPUS

Silicea HPUS

Purpose

Arsenicum album HPUS....................Worry
Arsenicum iodatum HPUS..................Fear
Calcarea carbonica HPUS..................Apprehension
Coffea cruda HPUS...........................Restlessness
Iodium, Ulmus procera, flos HPUS......Anxiety
Mancinella HPUS...............................Wandering thoughts
Physostigma venenosum HPUS..........Compulsive thoughts/behavior
Silicea HPUS......................................Obsessive thoughts/behavior

Each active ingredient contains equal volumes of 10X, 30X and LM1 potencies. The letters "HPUS" indicate that the components in this product are officially monographed in the Homeopathic Pharmacopoeia of the United States.

Product indications are based on Homeopathic Materia Medica.

Uses

to temporarily relieve symptoms commonly associated with obsessive compulsive disorder, such as:

- obsessive thoughts
- restlessness
- compulsive thoughts
- apprehension

Warnings

Ask a doctor before use if
• you are taking any other medications
• you have a medical condition

When using this product, use only as directed.

Stop use and ask a doctor if symptoms persist or worsen.

PREGNANCY OR BREAST FEEDING

If pregnant or breast-feeding, ask a health professional before use.

Keep out of the reach of children.

Directions

Dispense Compulsin directly into mouth, or add recommended dosage into 8-12 oz. of purified (non-chlorinated) water and drink. Safe for ages 2 and up.

DOSAGE BY WEIGHT
30-50 lbs 1/2 mL
(13.6-22.6 kg) twice per day
50+ lbs 1 mL
(22.6+ kg) twice per day

Other information

- do not use if tamper seal is broken
- store in a cool, dry place
- product must not come in contact with metal
- do not store next to electrical devices or appliances

Inactive ingredients

citric acid, potassium sorbate, purified ionized mineral water

Questions or comments?

You can email us at info@hellolife.net or call us toll-free at 1.800.875.0850
Monday through Friday 9am-5pm ET

DESCRIPTION

• 30-day supply
• dropper included
• Compulsin is made without alcohol or sugar. No gluten added.

Mftd for: HelloLife, Inc.
4460 44th St SE, Ste. C-600
Grand Rapids, MI 49512
FDA Pharmaceutical Establishment
#1053442, #3009727070
www.compulsin.com

Principal Display Panel

NDC 49726-034-02

COMPULSINTM

OCD* Symptom Relief
(*Obsessive Compulsive Disorder)
To temporarily relieve symptoms commonly associated with obsessive compulsive disorder, such as:
• obsessive thoughts
• restlessness
• compulsive thoughts
• apprehension

2 fl oz (59 mL)

Homeopathic (OTC) Medicine